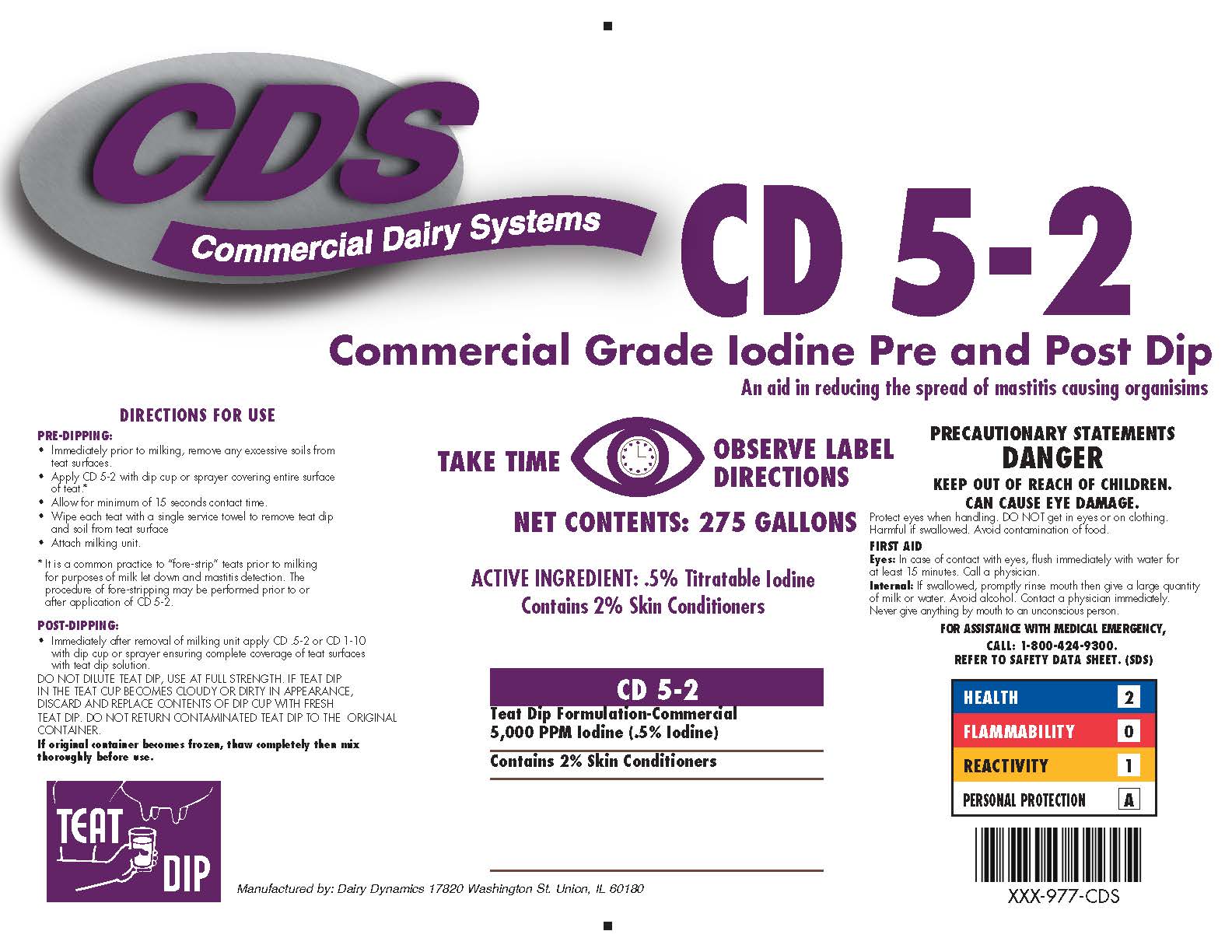 DRUG LABEL: CD 5-2
NDC: 62897-977 | Form: SOLUTION
Manufacturer: Brown Dairy Equipment
Category: animal | Type: OTC ANIMAL DRUG LABEL
Date: 20211208

ACTIVE INGREDIENTS: IODINE 5 g/1 L
INACTIVE INGREDIENTS: WATER; SORBITOL; C12-15 PARETH-9; XANTHAN GUM; POVIDONE K30; SODIUM HYDROXIDE; PHOSPHORIC ACID

CD 5-2
Commercial Grade Iodine Pre and Post Dip

ACTIVE INGREDIENT: .5% Titratable Iodine

Contains 2% Skin Conditioner

INDICATIONS AND USAGE

DIRECTIONS FOR USE

PRE-DIPPING

- Immediately prior to milking, remove any excessive soils from teat surfaces.
- Apply CD 5-2 with dip cup or sprayer covering entire surace of teat.*
- Allow for minimum of 15 seconds contact time.
- Wipe each teat with a single service towel to remove teat dip and soil from teat surface.
- Attach milking unit.

* It is a common practice to "fore-strip" teats prior to milking for purposes of milk let down and mastitis detection. The procedure of fore-stripping may be performed prior to or after application of CD 5-2.

POST-DIPPING

- Immediately after removal of milking unit apply CD 5-2 or CD 1-10 with dip cup or sprayer ensuring complete coverage of teat surfaces with teat dip solution.

DO NOT DILUTE TEAT DIP, USE AT FULL STRENGTH. IF TEAT DIP IN THE TEAT CUP BECOMES COLOUDY OR DIRTY IN APPEARANCE, DISCARD AND REPLACE CONTENTS OF DIP CUP WITH FRESH TEAT DIP. DO NOT RETURN CONTAMINATED TEAT DIP TO THE ORIGINAL CONTAINER.

If original container becomes frozen, thaw completely then mix thoroughly before use.

KEEP OUT OF REACH OF CHILDREN.

PRECAUTIONS

PRECAUTIONARY STATEMENTS

DANGER

CAN CAUSE EYE DAMAGE

Protect eyes when handling. DO NOT get in eyes or on clothing. Harmful if swallowed. Avoid contamination of food.

FIRST AID

Eyes: In case of contact with eyes, flush immediately with water for at least 15 minutes. Call a physician.

Internal: If swallowed, promptly rinse mouth then give a large quantity of milk or water. Avoid alcohol. Contact a physician immediately. Never give anything by mouth to an unconscious person.

FOR ASSISTANCE WITH MEDICAL EMERGENCY, CALL: 1-800-424-9300

REFER TO SAFETY DATA SHEET. (SDS)

HEALTH 2

FLAMMABIITY 0

REACTIVITY 1

PERSONAL PROTECTION A

Manufactured by: Dairy Dynamics 17820 Washington St. Union, IL 60180